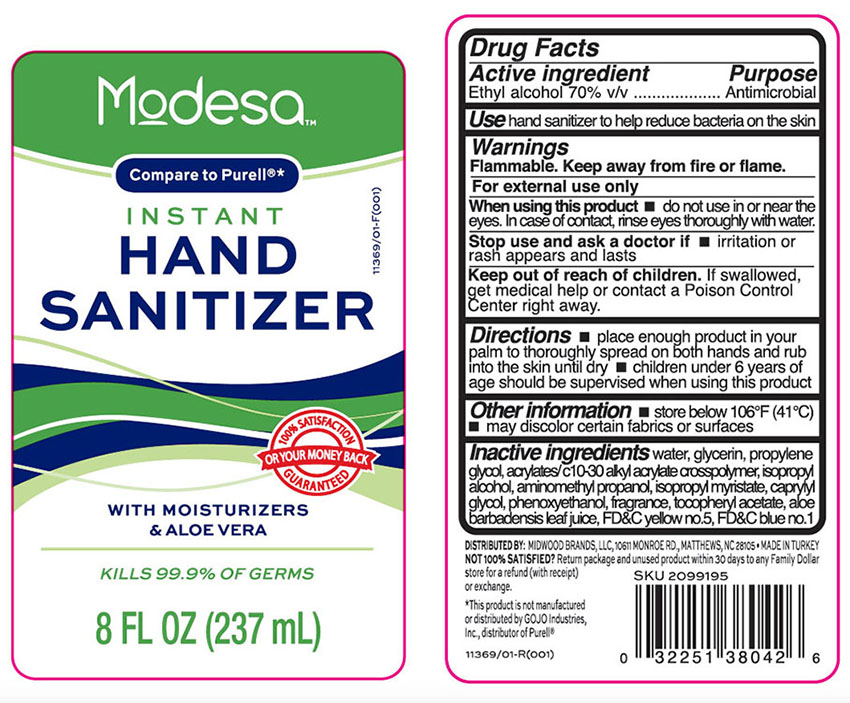 DRUG LABEL: Hand Sanitizer with Moisturizers and  Aloe Vera
NDC: 55319-432 | Form: LIQUID
Manufacturer: Family Dollar Services Inc.
Category: otc | Type: HUMAN OTC DRUG LABEL
Date: 20210115

ACTIVE INGREDIENTS: ALCOHOL 70 mL/100 mL
INACTIVE INGREDIENTS: ALOE VERA LEAF; CAPRYLYL GLYCOL; FD&C BLUE NO. 1; FD&C YELLOW NO. 5; GLYCERIN; ISOPROPYL ALCOHOL; ISOPROPYL MYRISTATE; AMINOMETHYLPROPANOL; PHENOXYETHANOL; PROPYLENE GLYCOL; .ALPHA.-TOCOPHEROL ACETATE; WATER; CARBOMER INTERPOLYMER TYPE A (ALLYL SUCROSE CROSSLINKED)

ModessaFmlyDlrHndSntzrAlchl70Aloe

Active ingredient

Ethyl Alcohol 70% v/v

Purpose

Antimicrobial

Use

hand sanitizer to help reduce bacteria on the skin

Warnings

Flammable. Keep away from fire and flame. For external use only

When using this product

■ do not use in or near the eyes. In case of contact, rinse eyes thoroughly with water.

Stop use and aska doctor if

■ irritation or rash appears and lasts

Keep out of reach of children

If swallowed, get medical help or contact a Poison Control Center right away.

Directions

■ place enough product in your palm to thoroughly spread on both hands and rub into the skin until dry. ■ children under 6 years of age should be supervised when using this product

Other information

■ store below 106ºF (41ºC) ■ may discolor certain fabrics or surfaces

Inactive ingredients

water, glycerin, propylene glycol, acrylates/c10-30 alkyl acrylate crosspolymer, isopropyl alcohol,aminomethylpropanol, isopropyl myristate, caprylyl glycol, phenoxyethanol, fragrance, tocopheryl acetate, aloe barbedensis leaf juice, FD&C yellow no. 5, FD&C blue no. 1